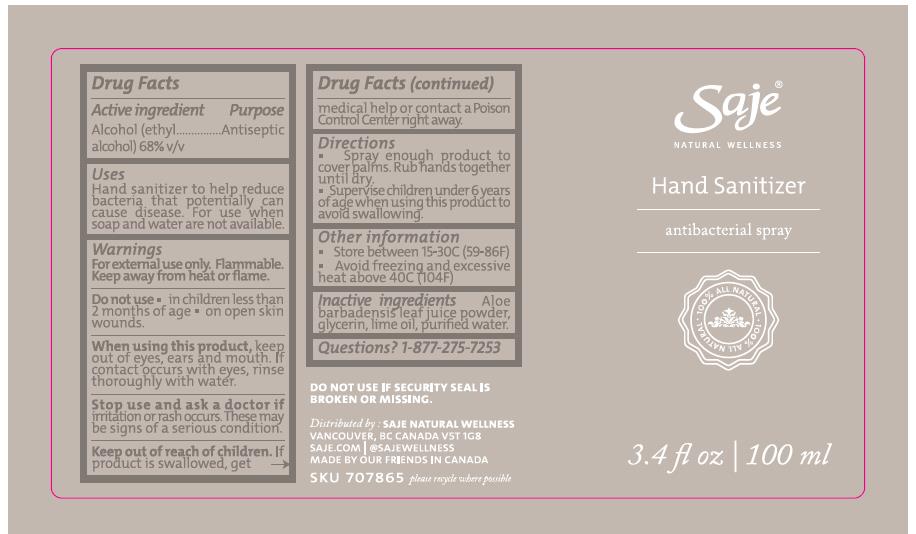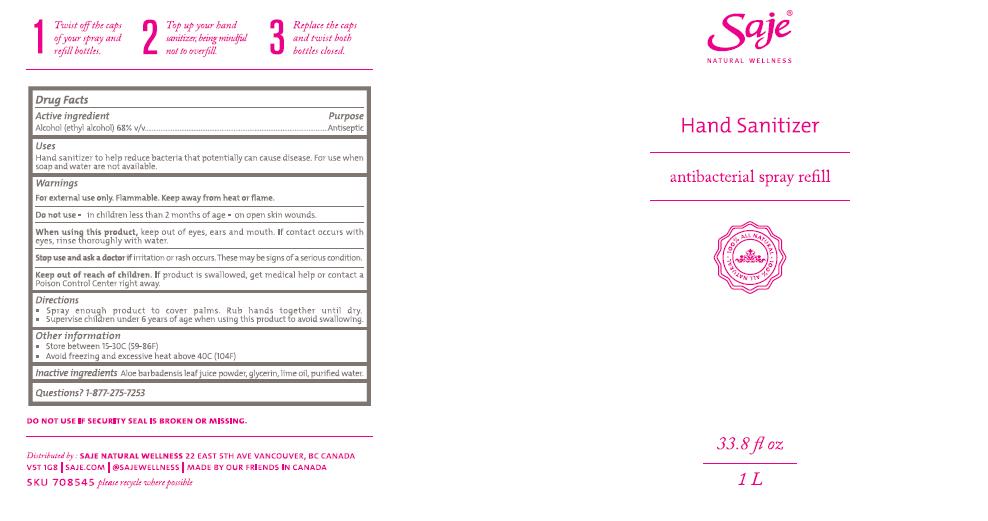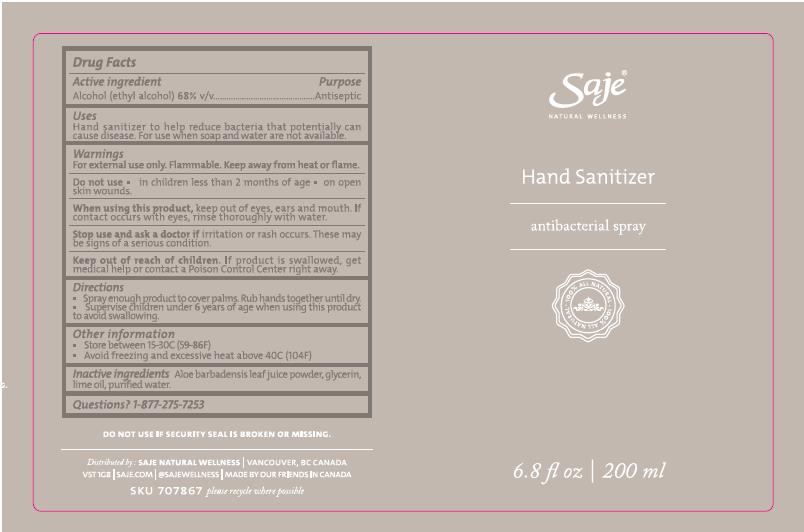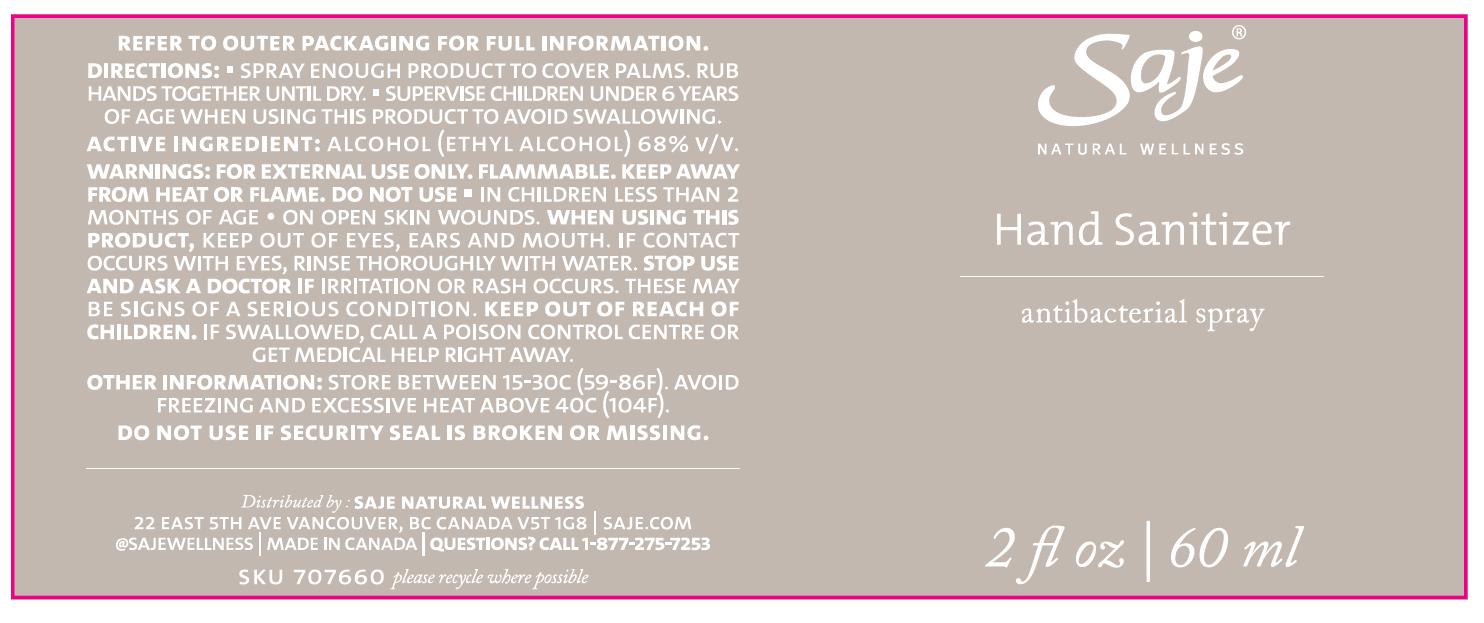 DRUG LABEL: Hand Sanitizer
NDC: 70983-025 | Form: SPRAY
Manufacturer: Saje Natural Business Inc.
Category: otc | Type: HUMAN OTC DRUG LABEL
Date: 20260113

ACTIVE INGREDIENTS: ALCOHOL 68 mL/100 mL
INACTIVE INGREDIENTS: LIME OIL; GLYCERIN; ALOE VERA LEAF; WATER

Hand Sanitizer

Active Ingredient(s)

Alcohol 68% v/v. Purpose: Antiseptic

Purpose

Antiseptic, Hand Sanitizer

Product Identity

Hand Sanitizer - Antibacterial Spray

2 fl oz | 60 ml

3.4 fl oz | 100 ml
6.8 fl oz | 200 ml
33.8 fl oz | 1 L

Use

Hand Sanitizer to help reduce bacteria that potentially can cause disease. For use when soap and water are not available.

Warnings

For external use only. Flammable. Keep away from heat or flame

Do not use

- in children less than 2 months of age
- on open skin wounds

When using this product keep out of eyes, ears, and mouth. If contact occurs with eyes, rinse thoroughly with water.
Stop use and ask a doctor if irritation or rash occurs. These may be signs of a serious condition.
Keep out of reach of children. If swallowed, contact a Poison Control Center right away or get medical help right away.

Stop use and ask a doctor if irritation or rash occurs. These may be signs of a serious condition.

Keep out of reach of children. If swallowed, get medical help or contact a Poison Control Center right away.

Directions

- Spray enough product on hands to cover all surfaces. Rub hands together until dry.
- Supervise children under 6 years of age when using this product to avoid swallowing.

Other information

- Store between 15-30C (59-86F)
- Avoid freezing and excessive heat above 40C (104F)

Inactive ingredients

aloe barbadensis leaf juice powder, glycerin, lime oil, purified water.

Hand Sanitizer Spray - Package Label

60 mL NDC: 70983-025-04

100 mL NDC: 70983-025-01

200 mL NDC: 70983-025-02

1 L NDC: 70983-025-03